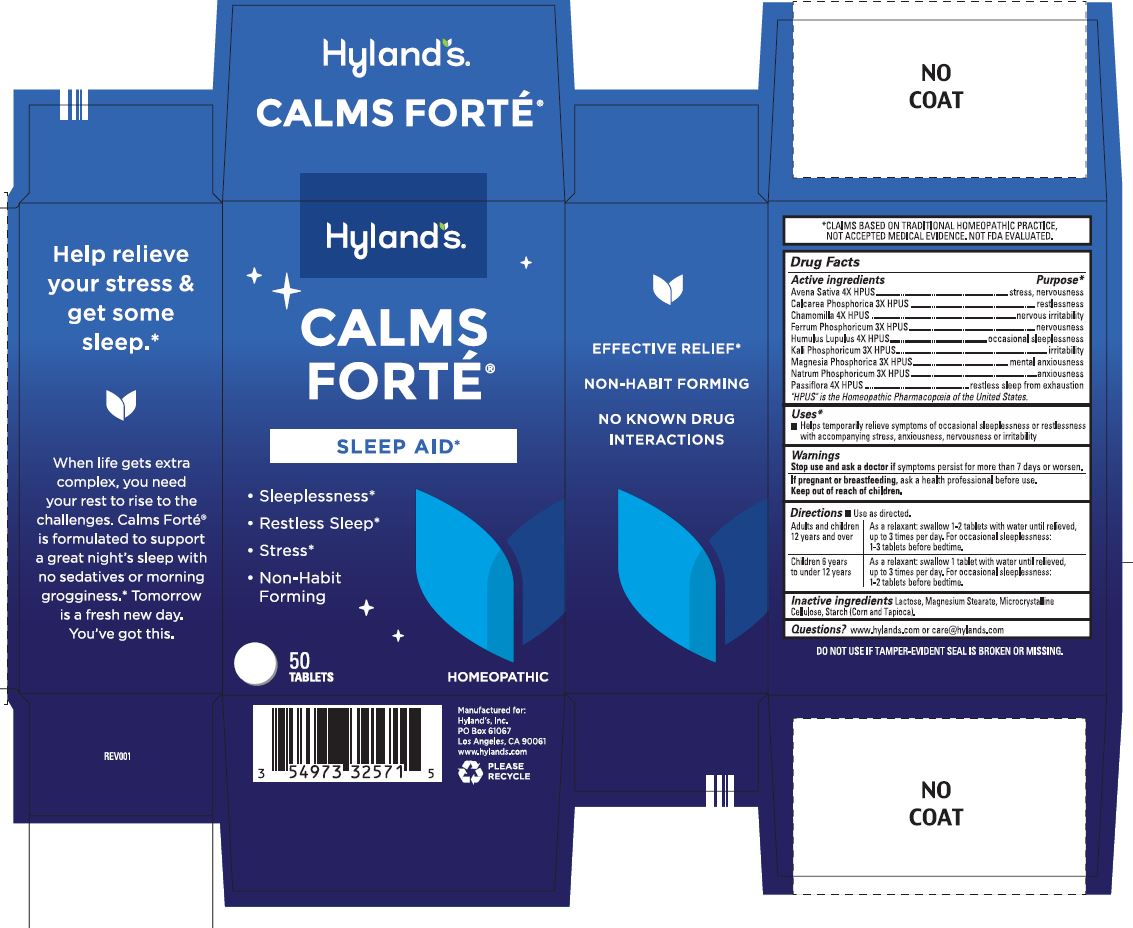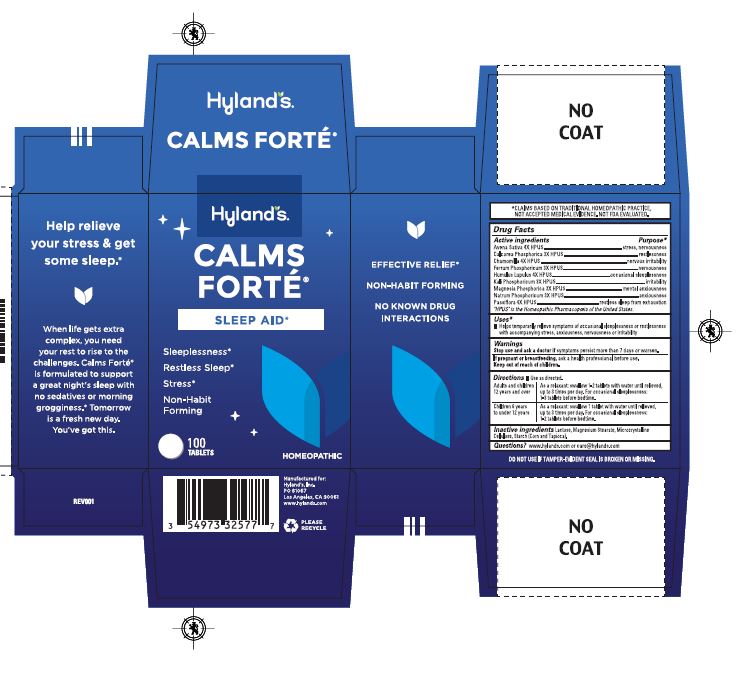 DRUG LABEL: CALMS FORTE
NDC: 54973-3257 | Form: TABLET
Manufacturer: Hyland's Inc.
Category: homeopathic | Type: HUMAN OTC DRUG LABEL
Date: 20250409

ACTIVE INGREDIENTS: AVENA SATIVA FLOWERING TOP 4 [hp_X]/1 1; TRIBASIC CALCIUM PHOSPHATE 3 [hp_X]/1 1; MATRICARIA RECUTITA 4 [hp_X]/1 1; FERROSOFERRIC PHOSPHATE 3 [hp_X]/1 1; HOPS 4 [hp_X]/1 1; POTASSIUM PHOSPHATE, DIBASIC 3 [hp_X]/1 1; MAGNESIUM PHOSPHATE, DIBASIC TRIHYDRATE 3 [hp_X]/1 1; SODIUM PHOSPHATE, DIBASIC, HEPTAHYDRATE 3 [hp_X]/1 1; PASSIFLORA INCARNATA FLOWER 4 [hp_X]/1 1
INACTIVE INGREDIENTS: LACTOSE, UNSPECIFIED FORM; MAGNESIUM PALMITOSTEARATE; CELLULOSE, MICROCRYSTALLINE; STARCH, CORN; STARCH, TAPIOCA

Calms Forte

Drug Facts

ACTIVE INGREDIENT

Active ingredients | Purpose
Avena Sativa 4X HPUS | stress, nervousness
Calcarea Phosphorica 3X HPUS | restlessness
Chamomilla 4X HPUS | nervous irritability
Ferrum Phosphoricum 3X HPUS | nervousness
Humulus Lupulus 4X HPUS | occasional sleeplessness
Kali Phosphoricum 3X HPUS | irritability
Magnesia Phosphorica 3X HPUS | mental anxiousness
Natrum Phosphoricum 3X HPUS | anxiousness
Passiflora 4X HPUS | restless sleep from exhaustion
"HPUS" indicates the active ingredients are in the official Homeopathic Pharmacopœia of the United States.

Uses

■ Temporarily relieves symptoms of occasional sleeplessness or restlessness with accompanying stress, anxiousness, nervousness or irritability

Warnings

Stop use and ask a doctor if

Symptoms persist more than 7 days or worsen.

If pregnant or breastfeeding

Ask a health professional before use.

Directions

■ Use as directed.

Adults and children 12 years and over | As a relaxant: swallow 1-2 tablets with water until relieved, up to 3 times per day. For occasional sleeplessness: 1-3 tablets before bedtime.
Children 6 years to under 12 years | As a relaxant: swallow 1 tablet with water until relieved, up to 3 times per day. For occasional sleeplessness: 1-2 tablets before bedtime.

Inactive ingredients

Lactose, Magnesium Stearate, Microcrystalline Cellulose, Starch (Corn and Tapioca).

Questions?

www.hylands.com or (800) 624-9659

Uses

occasional sleeplessness or restlessness with accompanying stress, anxiousness, nervousness and irritability. Changed "and" to "or"

RECENT MAJOR CHANGES

Dosage and Administration

Adults and children; 12 years and over | As a relaxant: swallow 1-2 tablets with water until relieved, up to 3 times; per day. For occasional sleeplessness: 1-3 tablets before bedtime.
Children 6 years; to under 12 years | As a relaxant: swallow 1 tablet with water until relieved, up to 3 times; per day. For occasional sleeplessness: 1-2 tablets before bedtime.

PRINCIPAL DISPLAY PANEL - 50 TABLET BOTTLE CARTON

Hyland's

NATURALS™

CALMS

FORTE®

SLEEP AID*

Sleeplessness

Restless Sleep

Stress

Non-Habit

Forming

50

TABLETS

HOMEOPATHIC